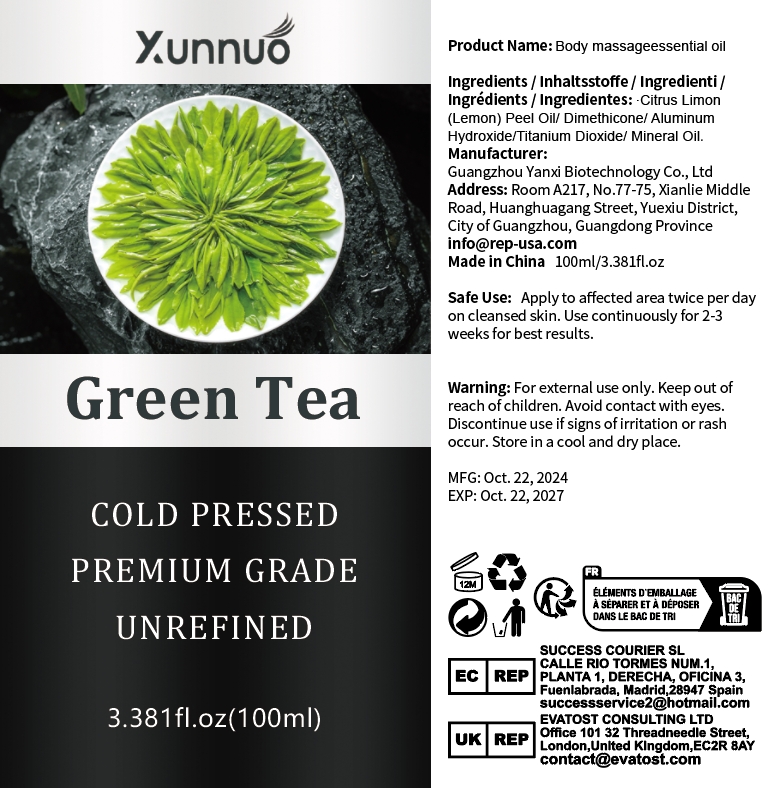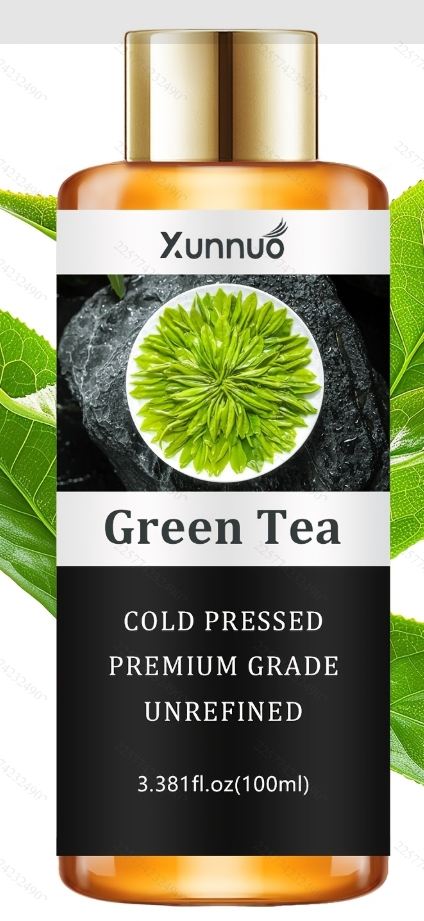 DRUG LABEL: Body massage essential oil
NDC: 84025-308 | Form: OIL
Manufacturer: Guangzhou Yanxi Biotechnology Co., Ltd
Category: otc | Type: HUMAN OTC DRUG LABEL
Date: 20250106

ACTIVE INGREDIENTS: DIMETHICONE 3 mg/100 mL; CITRUS LIMON (LEMON) PEEL OIL 5 mg/100 mL
INACTIVE INGREDIENTS: WATER

DOSAGE AND ADMINISTRATION

use as normal body oil

WARNINGS

keep out of children

INACTIVE INGREDIENT

Aqua

INDICATIONS AND USAGE

for daily body care

keep out of children

PURPOSE

Moisturize the body